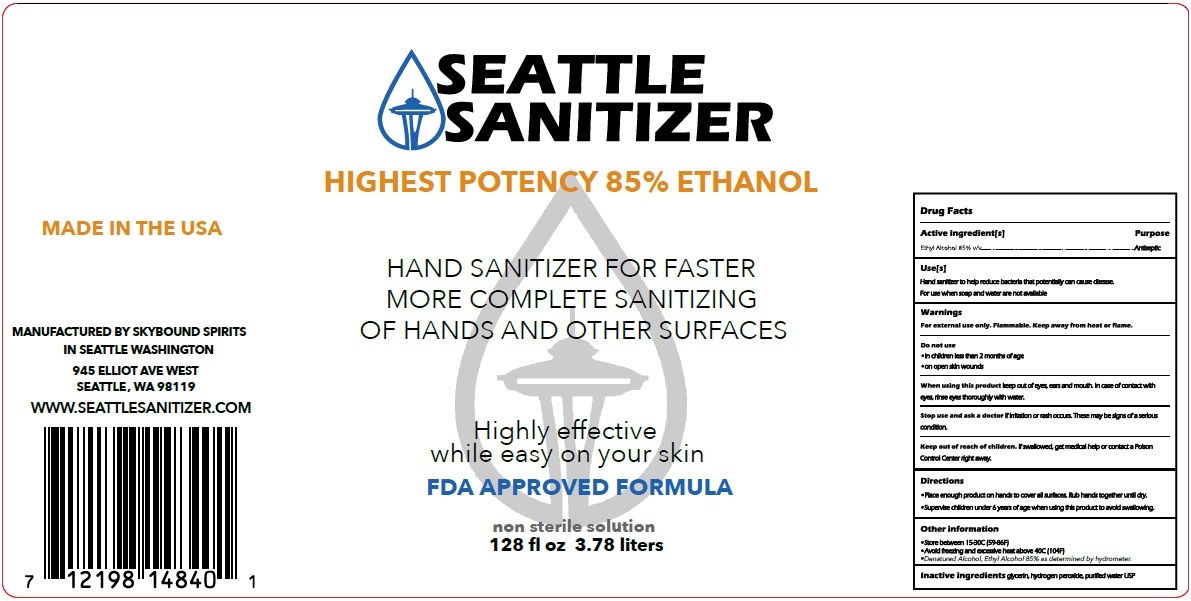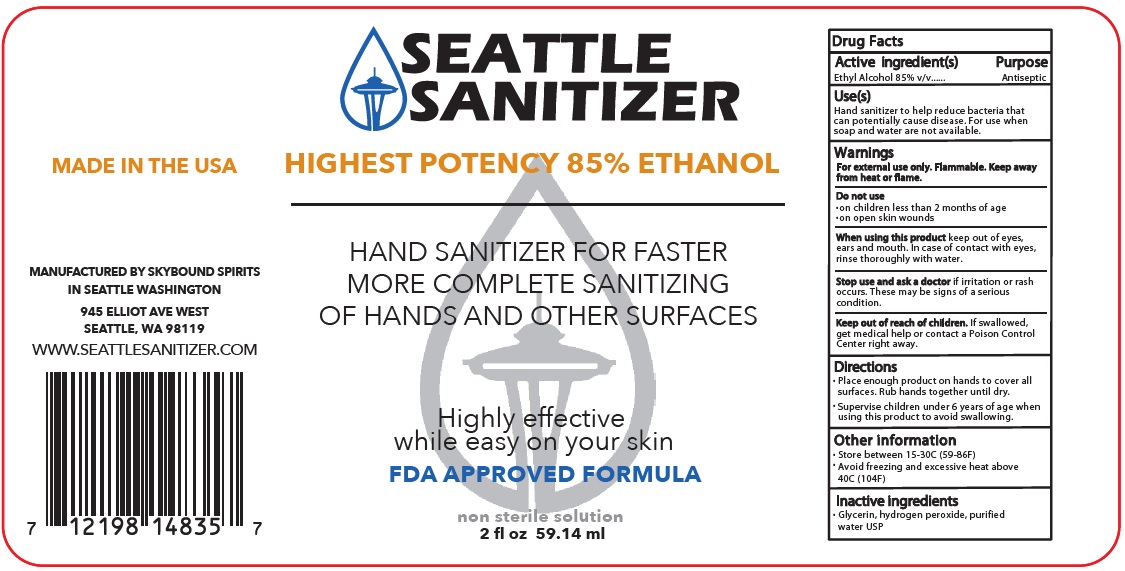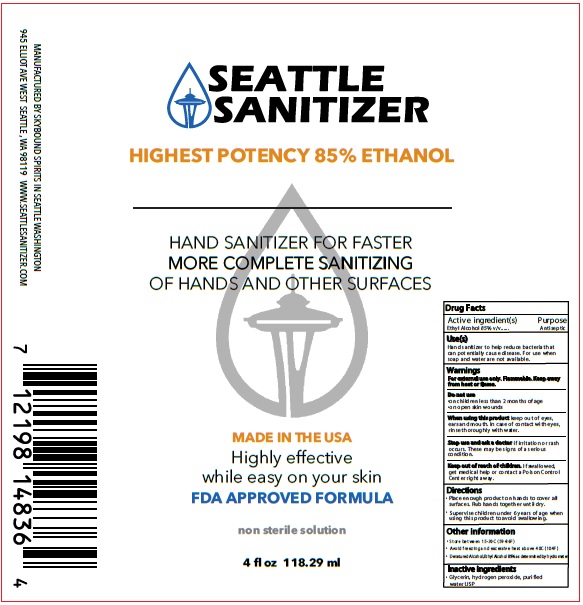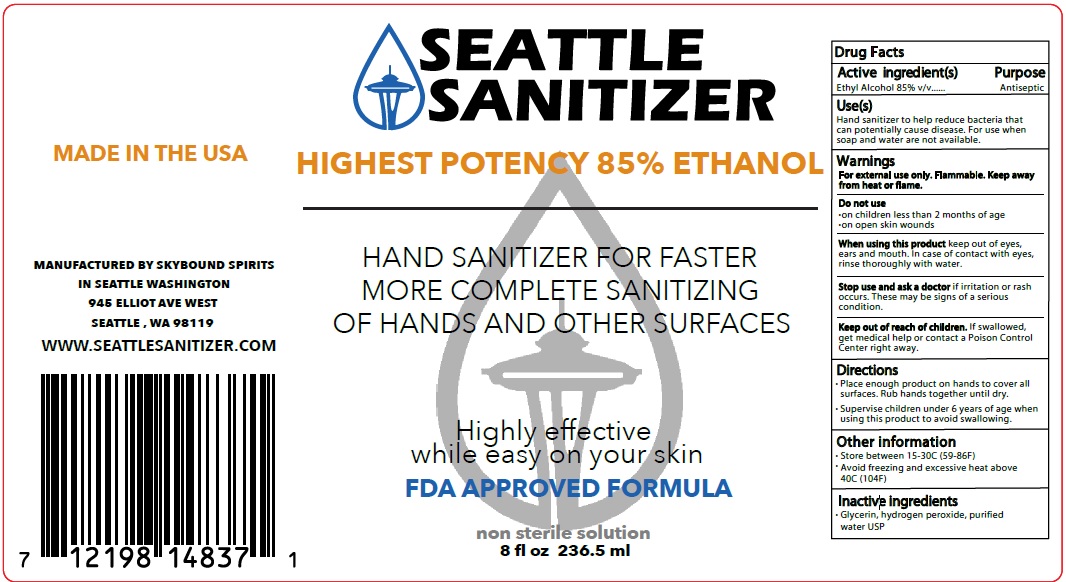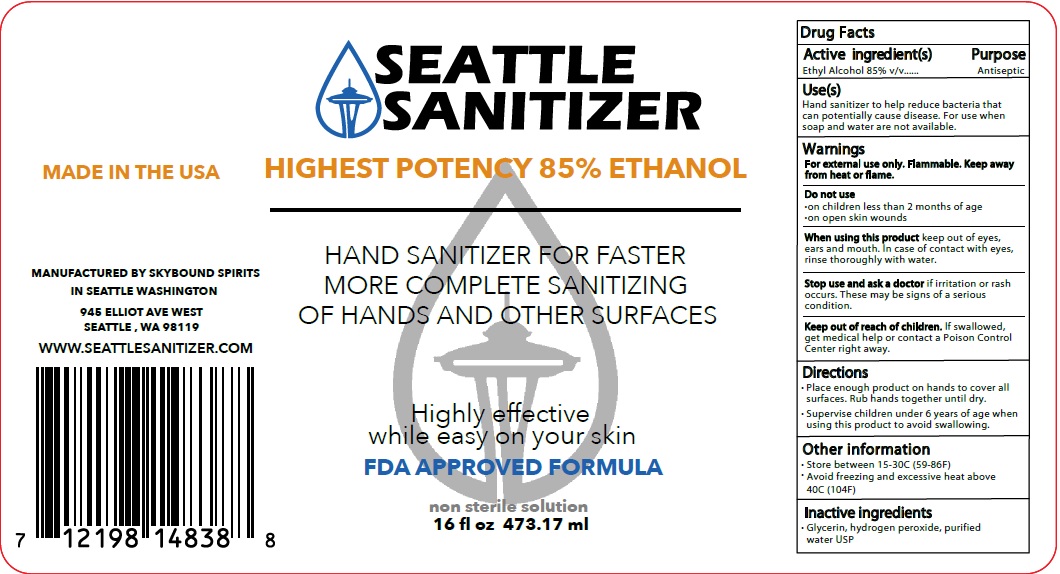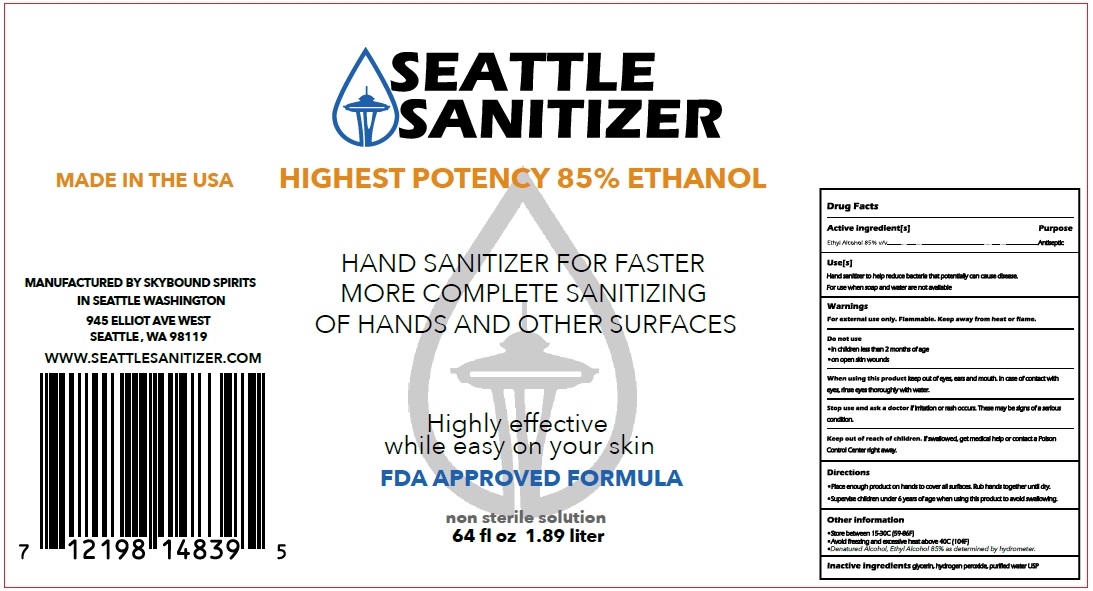 DRUG LABEL: Alcohol Based Hand Sanitizer
NDC: 78539-001 | Form: SOLUTION
Manufacturer: Seattle Sanitizer LLC
Category: otc | Type: HUMAN OTC DRUG LABEL
Date: 20200718

ACTIVE INGREDIENTS: ALCOHOL 85 mL/100 mL
INACTIVE INGREDIENTS: GLYCERIN; HYDROGEN PEROXIDE; WATER

SEATTLE SANITIZER

Active ingredient(s)

Ethyl Alcohol 85% v/v

Purpose

Antiseptic

Use(s)

Hand sanitizer to help reduce bacteria that potentially can cause disease. For use when soap and water are not available

Warnings

For external use only. Flammable. Keep away from heat or flame.

Do not use

• on children less than 2 months of age

• on open skin wounds
When using this product keep out of eyes, ears and mouth. In case of contact with eyes, rinse thoroughly with water.
Stop use and ask a doctor if irritation or rash occurs. These may be signs of a serious condition.

Keep out of reach of children. If swallowed, get medical help or contact a Poison Control Center right away.

Directions

- Place enough product on hands to cover all surfaces. Rub hands together until dry.
- Supervise children under 6 years of age when using this product to avoid swallowing.

Other information

- Store between 15-30C (59-86F)
- Avoid freezing and excessive heat above 40C (104F)
- Denatured Alcohol, Ethyl Alcohol 85% as determined by hydrometer.

Inactive ingredients glycerin, hydrogen peroxide, purified water USP

HIGHEST POTENCY 85% ETHANOL

HAND SANITIZER FOR FASTER MORE COMPLETE SANITIZING OF HANDS AND OTHER SURFACES

Highly effective while easy on your skin

FDA APPROVED FORMULA

non sterile solution

MADE IN THE USA

MANUFACTURED BY SKYBOUND SPIRITS
IN SEATTLE WASHINGTON
945 ELLIOT AVE WEST
SEATTLE, WA 98119

WWW.SEATTLESANITIZER.COM